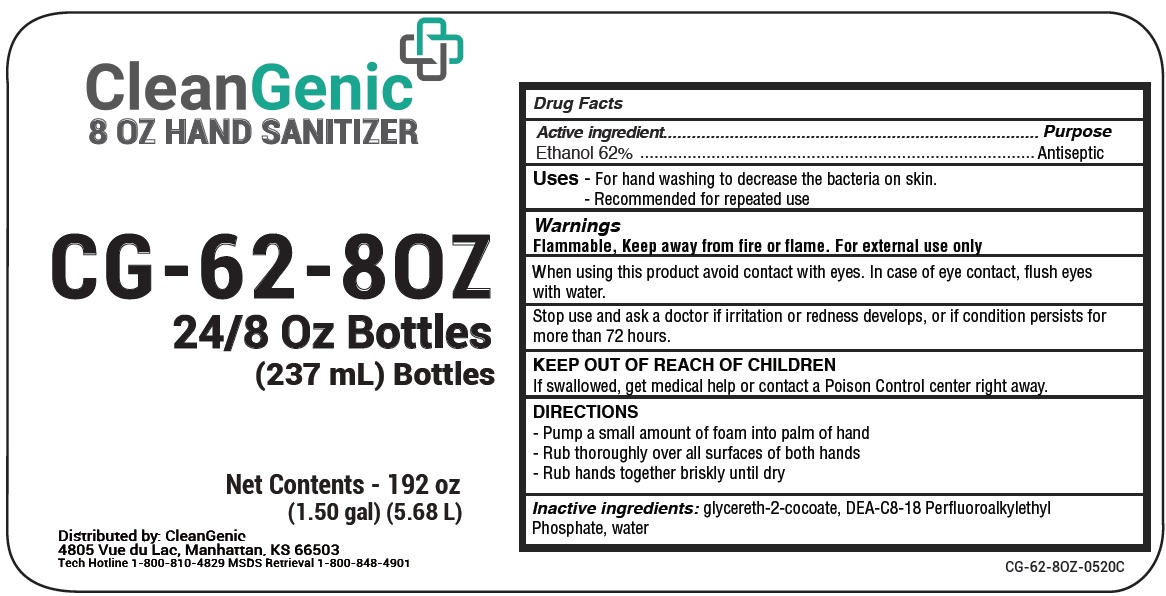 DRUG LABEL: CleanGenic Foaming Hand Sanitizer
NDC: 81385-002 | Form: LIQUID
Manufacturer: CleanGenic, LLC
Category: otc | Type: HUMAN OTC DRUG LABEL
Date: 20231028

ACTIVE INGREDIENTS: ALCOHOL 62 mL/100 mL
INACTIVE INGREDIENTS: WATER; GLYCERETH-2 COCOATE; DIETHANOLAMINE BIS(C8-C18 PERFLUOROALKYLETHYL)PHOSPHATE

CleanGenic Foaming Hand Sanitizer

Active ingredient

Ethanol 62%

Purpose

Antiseptic

Uses

- For hand washing to decrease the bacteria on skin. - Recommended for repeated use

Warnings

Flammable, keep away from fire or flame. For external use only

When using this product

avoid contact with eyes. In case of eye contact, flush eyes with water.

Stop use and ask a doctor if

irritation or redness develops, or if condition persists for more than 72 hours.

KEEP OUT OF REACH OF CHILDREN

If swallowed, get medical help or contact a Poison Control Center right away.

DIRECTIONS

- Pump a small amount of foam into palm of hand - Rub thoroughly over all surfaces of both hands - Rub hands together briskly until dry

Inactive ingredients:

Water, glycereth-2-cocoate, DEA-C8-18 Perfluoroalkylethyl Phosphate